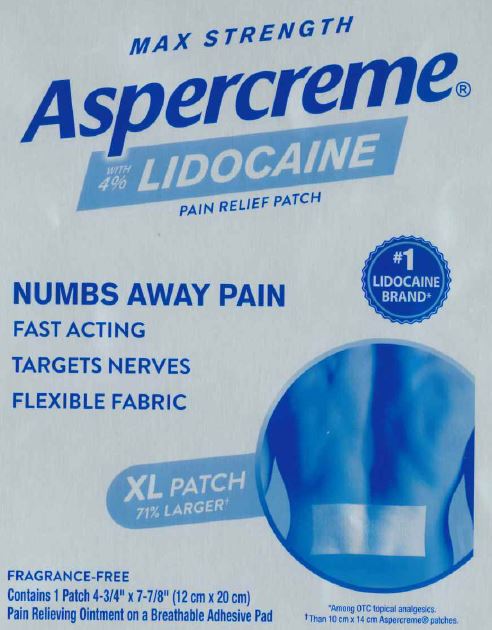 DRUG LABEL: Aspercreme
NDC: 62168-0585 | Form: PATCH
Manufacturer: Lead Chemical Co., Ltd.
Category: otc | Type: HUMAN OTC DRUG LABEL
Date: 20240102

ACTIVE INGREDIENTS: LIDOCAINE 411.4 mg/1 1
INACTIVE INGREDIENTS: DIHYDROXYALUMINUM AMINOACETATE ANHYDROUS; ALUMINUM HYDROXIDE; CARBOXYMETHYLCELLULOSE SODIUM, UNSPECIFIED FORM; GLYCERIN; METHYLPARABEN; NONOXYNOL-30; POLYSORBATE 80; PROPYLENE GLYCOL; SILICON DIOXIDE; TARTARIC ACID; TITANIUM DIOXIDE; UREA; WATER

Aspercreme Lidocaine XL Patch

Active ingredient

Lidocaine 4%

Purpose

Topical anesthetic

Use

for the temporary relief of pain

Warnings

For external use only

Do not use

- on puncture wounds, cuts, irritated or swollen skin
- more than 1 patch on your body at a time or with other topical analgesics at the same time
- with a heating pad or apply local heat to the area of use

When using this product

- use only as directed
- do not bandage tightly
- avoid contact with the eyes
- dispose of used patch in manner that always keeps product away from children and pets. Used patches still contain the drug product that can produce serious adverse effects if a child or pet chews or ingests this patch.

Stop use and ask a doctor if

- condition worsens or symptoms persist for more than 7 days
- symptoms clear up and occur again within a few days
- redness or irritation develops
- you experience signs of skin injury, such as pain, swelling, or blistering where the product was applied

If pregnant or breast-feeding,

ask a health professional before use.

Keep out of reach of children and pets.

If swallowed, get medical help or contact a Poison Control Center right away.

Directions

adults and children 12 years of age and older:

- clean and dry affected area
- remove backing from patch by firmly grasping both ends and gently pulling until backing separates in middle
- carefully remove smaller portion of backing from patch and apply exposed portion of patch to affected area
- once exposed portion of patch is positioned, carefully remove remaining backing to completely apply patch to affected area
- use 1 patch at a time and not more than 3 to 4 times daily

children 12 years or younger: consult a doctor

Inactive ingredients

aluminum glycinate, aluminum hydroxide, cellulose gum, glycerin, methyl acrylate/2-ethylhexyl acrylate copolymer, methylparaben, nonoxynol-30, polyacrylic acid, polysorbate 80, propylene glycol, silica, sodium polyacrylate, tartaric acid, titanium dioxide, urea, water

Package/Label Principal Display Panel

MAX STRENGTH

Aspercreme®
with 4% LIDOCAINE
PAIN RELIEF PATCH

NUMBS AWAY PAIN
FAST ACTING
TARGETS NERVES
FLEXIBLE FABRIC
#1 LIDOCAINE BRAND*

XL PATCH
71% LARGER†

FRAGRANCE-FREE
Contains 1 Patch 4-¾” x 7-7/8” (12 cm x 20 cm)
Pain Relieving Ointment on a Breathable Adhesive Pad

*Among OTC topical analgesics.
†Than 10 cm x 14 cm Aspercreme® patches.

CHATTEM®
A SANOFI COMPANY
Dist. By Chattem, Inc., a Sanofi Company
P.O. Box 2219, Chattanooga, TN
37409-0219 USA
©2020
www.aspercreme.com Made in Japan

Label